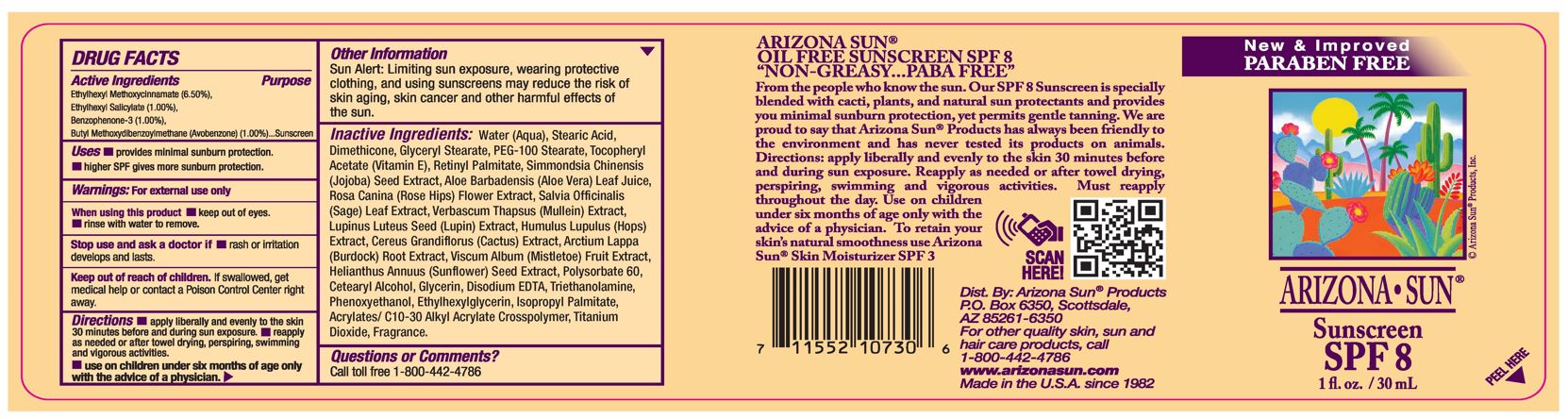 DRUG LABEL: Arizona Sun Sunscreen SPF 8
NDC: 61973-113 | Form: LOTION
Manufacturer: Arizona Sun Products
Category: otc | Type: HUMAN OTC DRUG LABEL
Date: 20240221

ACTIVE INGREDIENTS: AVOBENZONE 10 mg/1 g; OCTISALATE 10 mg/1 g; OCTINOXATE 65 mg/1 g; OXYBENZONE 10 mg/1 g
INACTIVE INGREDIENTS: ISOPROPYL PALMITATE; SELENICEREUS GRANDIFLORUS FLOWER; SUNFLOWER SEED; SIMMONDSIA CHINENSIS SEED; ETHYLHEXYLGLYCERIN; POLYSORBATE 60; STEARIC ACID; GLYCERYL STEARATE SE; PEG-100 STEARATE; GLYCERIN; DIMETHICONE; ROSA CANINA FLOWER; PHENOXYETHANOL; SAGE; ALOE VERA LEAF; STEARYL ALCOHOL; VITAMIN A PALMITATE; TITANIUM DIOXIDE; WATER; .ALPHA.-TOCOPHEROL ACETATE; DISODIUM EDTA-COPPER; LUPINUS LUTEUS SEED; HOPS; TROLAMINE; MULLEIN LEAF; ARCTIUM LAPPA ROOT; VISCUM ALBUM FRUIT; ACRYLATES/C10-30 ALKYL ACRYLATE CROSSPOLYMER (60000 MPA.S)

1 oz SPF 8

Active Ingredients

Ethylhexyl Methoxycinnamate (6.50%), Ethylhexyl Salicylate (1.00%), Benzophenone-3 (1.00%), Butyl Methoxydibenzoylmethane (1.00%)

Purpose

Sunscreen

Uses

Provides minimal sunburn protection. Higher SPF gives more sunburn protection.

Warnings

For external use only.

When using this product

keep out of eyes. Rinse with water to remove.

Stop use and ask a doctor if

if rash or irritation develops and lasts.

Keep out of the reach of children.

If swallowed get medical help or contact a poison control center right away.

Directions

Apply liberally and evenly to the skin 30 minutes before and during sun exposure. Reapply as needed or after towel drying, perspiring, swimming, and vigorous activities. Use on childen under the age of 6 months only wih the advise of a physician.

Other Information

Sun Alert: Limiting sun exposure, wearing protective clothing, and using suscreen may reduce the risk of skin aging, skin cancer and other harmful effects of the sun.

Inactive Ingredients

Water, Isopropyl Palmitate, Stearic Acid, Glyceryl Stearate, PEG-100 Stearate, Glycerin, Dimethicone, Cetearyl Alcohol, Tocopheryl Acetate (Vitamin E), Retinyl Palmitate, Simmondsia Chinensis (Jojoba) Seed Oil, Polysorbate 60, Aloe Barbadensis (Aloe Vera) Leaf Juice, Rosa Canina (Rose Hips) Flower Extract, Salvia Officinalis (Sage) Leaf Extract, Verbascum Thapsus (Mullein) Extract, Lupinus Luteus Seed (Lupin) Extract, Humulus Lupulus (Hops) Extract, Cereus Grandiflorus (Cactus) Extract, Arctium Lappa (Burdock) Root Extract, Viscum Album (Mistletoe) Fruit Extract, Helianthus Annuus (Sunflower) Seed Extract, Acrylates/ C10-30 Alkyl Acrylate Crosspolymer, Disodium EDTA, Triethanolamine, Phenoxyethanol, Ethylhexylglycerin, Fragrance , Titanium Dioxide

Questions or Comments?

Call toll free 1-800-442-4786